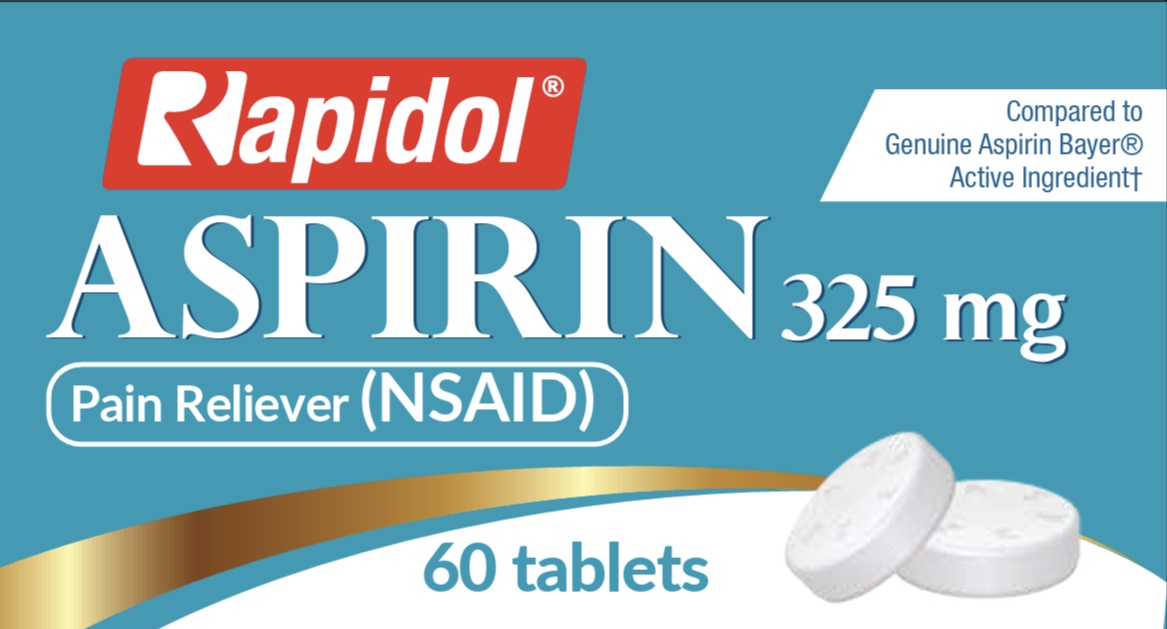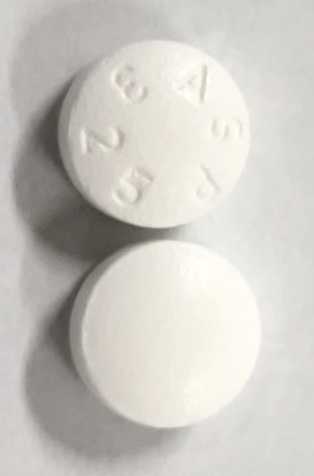 DRUG LABEL: Rapidol Aspirin
NDC: 55758-363 | Form: TABLET, COATED
Manufacturer: Pharmadel LLC
Category: otc | Type: HUMAN OTC DRUG LABEL
Date: 20250714

ACTIVE INGREDIENTS: ASPIRIN 325 mg/1 1
INACTIVE INGREDIENTS: POLYVINYL ALCOHOL, UNSPECIFIED; STARCH, CORN; POLYETHYLENE GLYCOL, UNSPECIFIED; MICROCRYSTALLINE CELLULOSE; TITANIUM DIOXIDE; POVIDONE; HYPROMELLOSE, UNSPECIFIED; TALC; SILICON DIOXIDE

Rapidol Aspirin 325 mg (HPUSA)

Active ingredient and Purpose

.

Active ingredient; (in each tablet) | Purpose
Aspirin 325 mg (NSAID*).............................; *nonsteroidal anti-inﬂammatory drug | Pain reliever

Uses

Temporary relief of minor aches and pains due to:

- a cold
- headache
- backache
- muscular aches
- toothache
- minor pains from arthritis

Warnings

Reye's syndrome: Children and teenagers who have or are recovering from chicken pox or flu-like symptoms should not use this product. When using this product, if changes in behavior with nausea and vomiting occur, consult a doctor because these symptoms could be an early sign of Reye's syndrome, a rare but serious illness.

Allergy alert: Aspirin may cause severe allergic reactions which may include:

■ hives

■ facial swelling

■ shock

■ asthma (wheezing)

Stomach bleeding warning: This product contains an NSAID, which may cause severe stomach bleeding. The chance is higher if you: ■ are age 60 or older ■ have had stomach ulcers or bleeding problems ■ take a blood thinning (anticoagulant) or steroid drug ■ take other drugs containing prescription or nonprescription NSAIDs (aspirin, ibuproben, naproxen, or others) ■ have 3 or more alcoholic drinks every day while using this product ■ take more or for a longer time than directed

Do not use

■ if you have ever had an allergic reaction to any other pain reliever/fever reducer

Ask a doctor before use if

■ you have asthma ■ stomach bleeding warning applies to you ■ you have a history of stomach problems, such as heartburn ■ you have high blood pressure, heart disease, liver cirrhosis, or kidney disease ■ you take a diuretic

Ask a doctor or pharmacist before use if you are

■ taking a prescription drug for diabetes, gout, or arthritis

Stop use and ask a doctor if

■ an allergic reaction occurs. Seek medical help right away. ■ you experience any of the following signs of stomach bleeding:

■ feel faint

■ vomit blood

■ have bloody or black stools

■ have stomach pain that does not get better

■ ringing in the ears or a loss of hearing occurs

■pain gets worse or last for more than 10 days

■ fever gets worse or lasts more than 3 days

■ redness or swelling is present

■ any new symptoms appear

If pregnant or breast-feeding,

ask a health professional before use. It is especially important not to use aspirin during the last 3 months of pregnancy unless definitely directed to do so by a doctor because it may cause problems in the unborn child or complications during delivery.

Keep out of reach of children.

In case of an overdose, get medical help or contact a Poison Control Center right away.

Directions

■adults and children 12 years of age and older:

■ drink a full glass of water with each dose

■ take one (1) or two (2) tablets every 4 hours, while symptoms persist

■ do not take more than 12 tablets in 24 hours, unless directed by a doctor

■children under 12 years of age: consult a doctor

Other information

- store between 68-77˚F (20-25˚C)

Inactive ingredients

corn starch, hypromellose, microcrystalline cellulose, polyethylene glycol, polyvinyl alcohol, povidone, silicon dioxide, talc, titanium dioxide

Questions or comments?

Dist. by/ por: Pharmadel LLC

New Castle, DE 19720

+1-866-359-3478

(M-F) 9AM to 5 PM EST or www.pharmadel.com